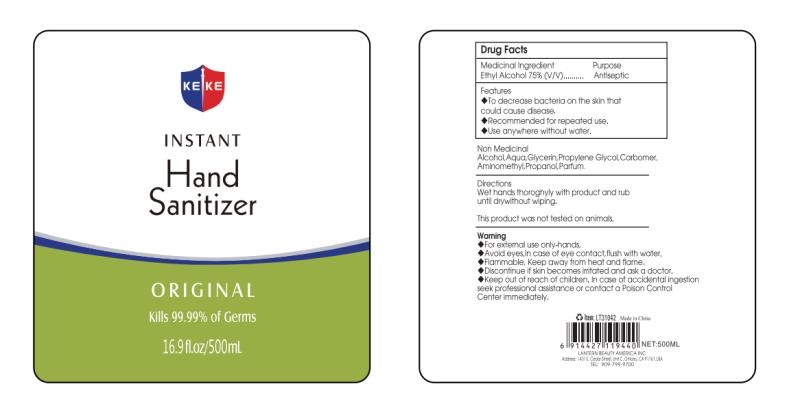 DRUG LABEL: KEKE HAND SANITIZER
NDC: 70415-511 | Form: GEL
Manufacturer: CWGC LA Inc.
Category: otc | Type: HUMAN OTC DRUG LABEL
Date: 20230921

ACTIVE INGREDIENTS: ALCOHOL 75 mL/100 mL
INACTIVE INGREDIENTS: WATER; GLYCERIN; PROPYLENE GLYCOL; CARBOMER INTERPOLYMER TYPE A (ALLYL SUCROSE CROSSLINKED); AMINOMETHYLPROPANOL

CWGC - KEKE HAND SANITIZER 75% (70415-511)

Active ingredient

Ethyl Alcohol 75% (V/V)

PURPOSE

ANTISEPTIC

Uses

- TO DECREASE BACTERIA ON THE SKIN THAT COULD CAUSE DISEASE.
- RECOMMEND FOR REPEATED USE.
- USE ANYWHERE WITHOUT WATER.

Warnings

- For external use only - hands.
- Avoid eyes. In case of eye contact, flush with water.
- Flammable. Keep away from fire or flame.
- Discontinue if skin becomes irritated and ask a doctor.

WHEN USING

When using this productavoid contact with eyes. In case of eye contact, flush with water

Keep out of reach of children. If swallowed, get medical help or contact a Poison Control Center right away.

Keep out of reach of children. In case of accidental ingestion seek professional assistance or contact a Poison Control Center immediately.

Directions

Wet hands thoroughly with product and rub until dry without wiping.

OTHER SAFETY INFORMATION

This product was not tested on animals.

Non Medicinal

ALCOHOL, AQUA, GLYCERIN, PROPYLENE GLYCOL, CARBOMER, AMINOMETHYL PROPANOL, PARFUM.